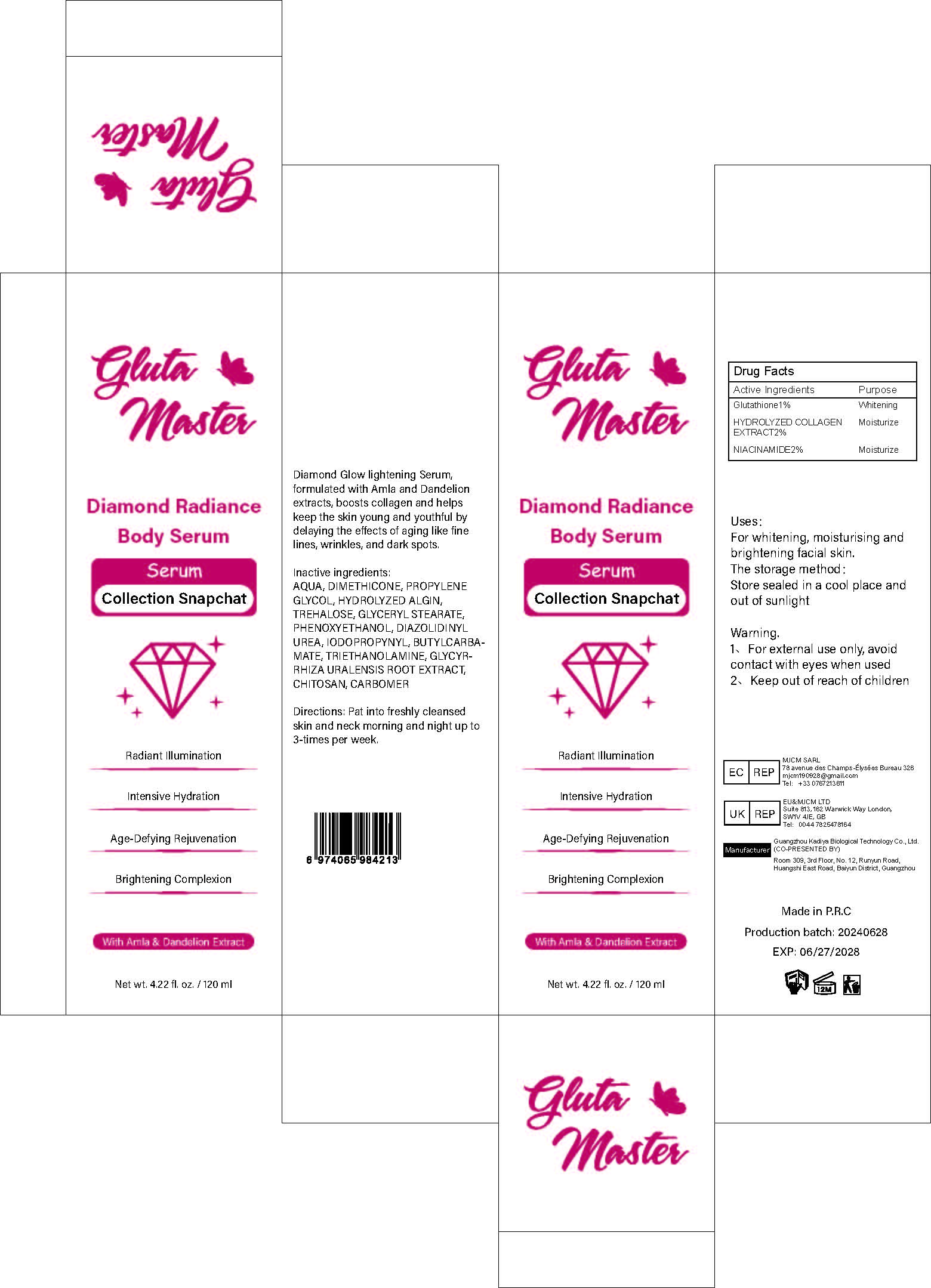 DRUG LABEL: Diamond Radiance Body Serum
NDC: 84423-019 | Form: LIQUID
Manufacturer: Guangzhou Kadiya Biotechnology Co., Ltd.
Category: otc | Type: HUMAN OTC DRUG LABEL
Date: 20240709

ACTIVE INGREDIENTS: NIACINAMIDE 2.4 mg/120 mg; GLUTATHIONE 1.2 mg/120 mg
INACTIVE INGREDIENTS: WATER; TREHALOSE; IODOPROPYNYL BUTYLCARBAMATE; TROLAMINE; PROPYLENE GLYCOL; CARBOXYPOLYMETHYLENE; DIAZOLIDINYL UREA; DIMETHICONE; PHENOXYETHANOL; POLIGLUSAM; GLYCYRRHIZA GLABRA; GLYCERYL MONOSTEARATE

Uses：
For whitening, moisturising and brightening facial skin.

INACTIVE INGREDIENT

AQUA、DIMETHICONE、PROPYLENE GLYCOL、HYDROLYZED ALGIN、TREHALOSE、GLYCERYL STEARATE、PHENOXYETHANOL、DIAZOLIDINYL UREA、IODOPROPYNYL、BUTYLCARBAMATE、TRIETHANOLAMINE、GLYCYRRHIZA URALENSIS ROOT EXTRACT、CHITOSAN、CARBOMER

Warning.
1、For external use only, avoid contact with eyes when used
2、Keep out of reach of children

INDICATIONS AND USAGE

Pat into freshly cleansed skin and neck morning and night up to 3-times per week.

KEEP OUT OF REACH OF CHILDREN SECTION

Active Ingredients
Glutathione 1%
HYDROLYZED COLLAGEN EXTRACT 2%
NIACINAMIDE 2%

DOSAGE AND ADMINISTRATION

Pat into freshly cleansed skin and neck morning and night up to 3-times per week.

PACKAGE LABEL

Active Ingredients
Glutathione 1%
HYDROLYZED COLLAGEN EXTRACT 2%
NIACINAMIDE 2%

Uses：
For whitening, moisturising and brightening facial skin.
Indications: For whitening, moisturising and brightening facial skin.
The storage method：
Store sealed in a cool place and out of sunlight

Warning.
1、For external use only, avoid contact with eyes when used
2、Keep out of reach of children

Inactive ingredients：
AQUA、DIMETHICONE、PROPYLENE GLYCOL、HYDROLYZED ALGIN、TREHALOSE、GLYCERYL STEARATE、PHENOXYETHANOL、DIAZOLIDINYL UREA、IODOPROPYNYL、BUTYLCARBAMATE、TRIETHANOLAMINE、GLYCYRRHIZA URALENSIS ROOT EXTRACT、CHITOSAN、CARBOMER